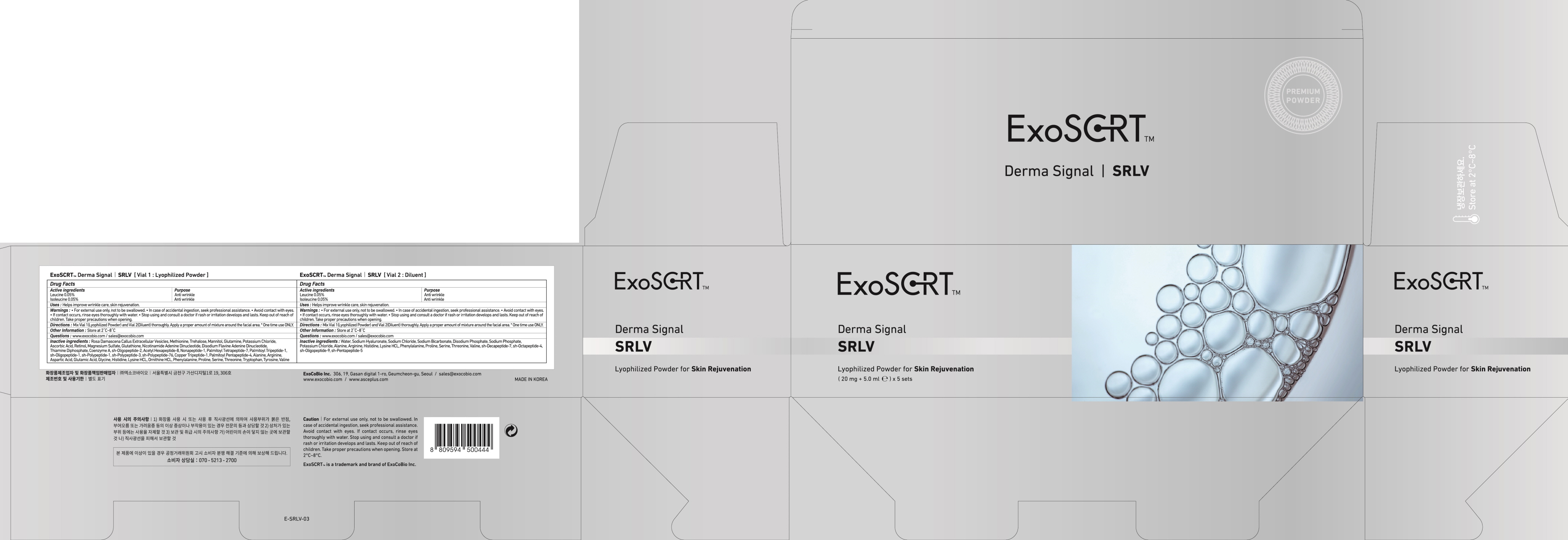 DRUG LABEL: ExoSCRT Derma Signal SRLV Vial 1. Lyophilized
NDC: 72951-140 | Form: POWDER
Manufacturer: Exocobio Inc.
Category: otc | Type: HUMAN OTC DRUG LABEL
Date: 20241209

ACTIVE INGREDIENTS: LEUCINE 0.01 mg/20 mg; ISOLEUCINE 0.01 mg/20 mg
INACTIVE INGREDIENTS: METHIONINE; TREHALOSE

ACTIVE INGREDIENT

Leucine 0.05%
Isoleucine 0.05%

INACTIVE INGREDIENTS

Rosa Damascena Callus Extracellular Vesicles, Methionine, Trehalose, Mannitol, Glutamine, Potassium Chloride, Ascorbic Acid, Retinol, Magnesium Sulfate, Glutathione, Nicotinamide Adenine Dinucleotide, Disodium Flavine, Adenine Dinucleotide, Thiamine Diphosphate, Coenzyme A, sh-Oligopeptide-2, Acetyl Hexapeptide-8, Nonapeptide-1, Palmitoyl Tetrapeptide-7, Palmitoyl Tripeptide-1, sh-Oligopeptide-1, sh-Polypeptide-1, sh-Polypeptide-3, sh-Polypeptide-76, Copper Tripeptide-1, Palmitoyl Pentapeptide-4, Alanine, Arginine, Aspartic Acid, Glutamic Acid, Glycine, Histidine, Lysine HCL, Ornithine HCL, Phenylalanine, Proline, Serine, Threonine, Tryptophan, Tyrosine, Valine

PURPOSE

Anti wrinkle

WARNINGS

For external use only, not to be swallowed.
In case of accidental ingestion, seek professional assistance.
Avoid contact with eyes.
If contact occurs, rinse eyes thoroughly with water.
Stop using and consult a doctor if rash or irritation develops and lasts. Keep out of reach of children. Take proper precautions when opening.

KEEP OUT OF REACH OF CHILDREN

Uses

■ Helps improve wrinkle care, skin rejuvenation.

Directions

■ Mix Vial 1(Lyophilized Powder) and Vial 2(Diluent) thoroughly.
Apply a proper amount of mixture around the facial area.
* One time use ONLY.

Other Information

Store at 2℃~8℃

Questions

www.exocobio.com / sales@exocobio.com